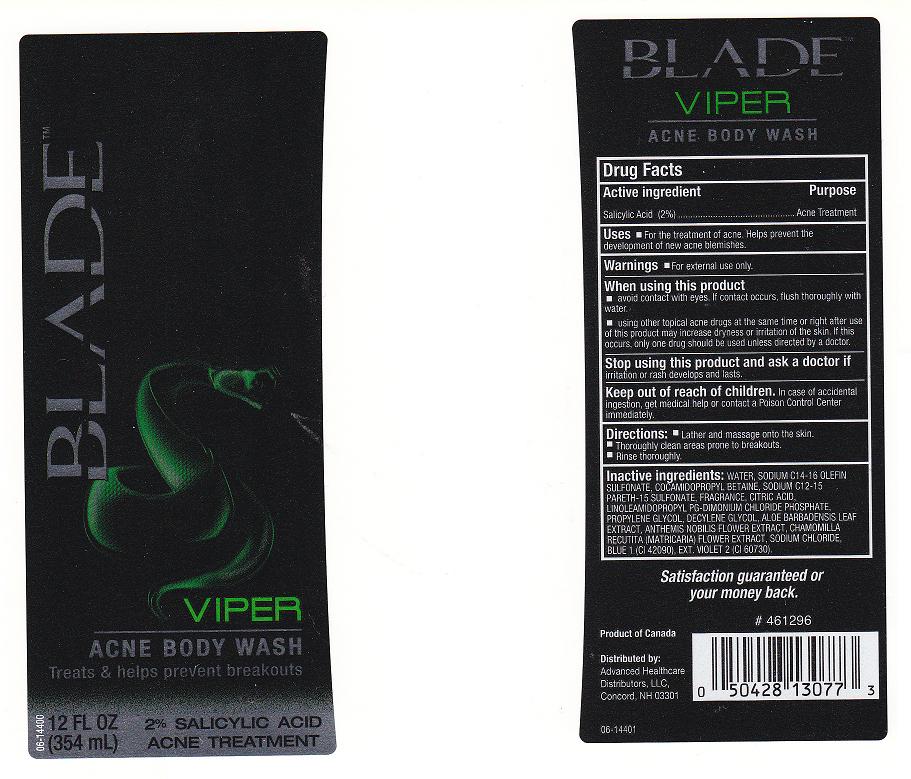 DRUG LABEL: VIPER ACNE BODY WASH
NDC: 59779-806 | Form: LIQUID
Manufacturer: CVS PHARMACY
Category: otc | Type: HUMAN OTC DRUG LABEL
Date: 20110318

ACTIVE INGREDIENTS: SALICYLIC ACID 2 mL/100 mL
INACTIVE INGREDIENTS: WATER; SODIUM C14-16 OLEFIN SULFONATE; COCAMIDOPROPYL BETAINE; SODIUM C12-15 PARETH-15 SULFONATE; ANHYDROUS CITRIC ACID; LINOLEAMIDOPROPYL PG-DIMONIUM CHLORIDE PHOSPHATE; PROPYLENE GLYCOL; 1-DECENE; ALOE VERA LEAF; CHAMAEMELUM NOBILE FLOWER; CHAMOMILE; SODIUM CHLORIDE; FD&C BLUE NO. 1; EXT. D&C VIOLET NO. 2

DRUG FACTS

ACTIVE INGREDIENT

SALICYLIC ACID 2%

PURPOSE

ACNE TREATMENT

USES

FOR THE TREATMENT OF ACNE. HELPS PREVENT THE DEVELOPMENT OF NEW ACNE BLEMISHES.

WARNINGS

FOR EXTERNAL USE ONLY.

WHEN USING THIS PRODUCT

AVOID CONTACT WITH EYES. IF CONTACT OCCURS, FLUSH THOROUGHLY WITH WATER.

USING OTHER TOPICAL ACNE DRUGS AT THE SAME TIME OR RIGHT AFTER USE OF THIS PRODUCT MAY INCREASE DRYNESS OR IRRITATION OF THE SKIN. IF THIS OCCURS, ONLY ONE DRUG SHOULD BE USED UNLESS DIRECTED BY A DOCTOR.

STOP USING THIS PRODUCT AND ASK A DOCTOR IF

IRRITATION OR RASH DEVELOPS AND LASTS.

KEEP OUT OF REACH OF CHILDREN

Enter section text here

DIRECTIONS:

Enter section text here

INACTIVE INGREDIENTS

WATER, SODIUM LAURETH SULFAE, SODIUM C14-16 OLEFIN SULFONATE, COCAMIDOPROPYL BETAINE, SODIUM C12-15 PARETH-15 SULFONATE, FRAGRANCE, CITRIC ACID, LINOLEAMIDOPROPYL PG-DIMONIUM CHLORIDE PHOSPHATE, PROPYLENE GLYCOL, DECYLENE GLYCOL, ALOE BARBADENSIS LEAF EXTRACT, ANTHEMIS NOBILIS FLOWER EXTRACT, CHAMOMILLA RECUTITA (MATRICARIA) FLOWER EXTRACT, SODIUM CHLORIDE, BLUE 1 (CI 42090), EXT.VIOLET 2 (CI 60730).